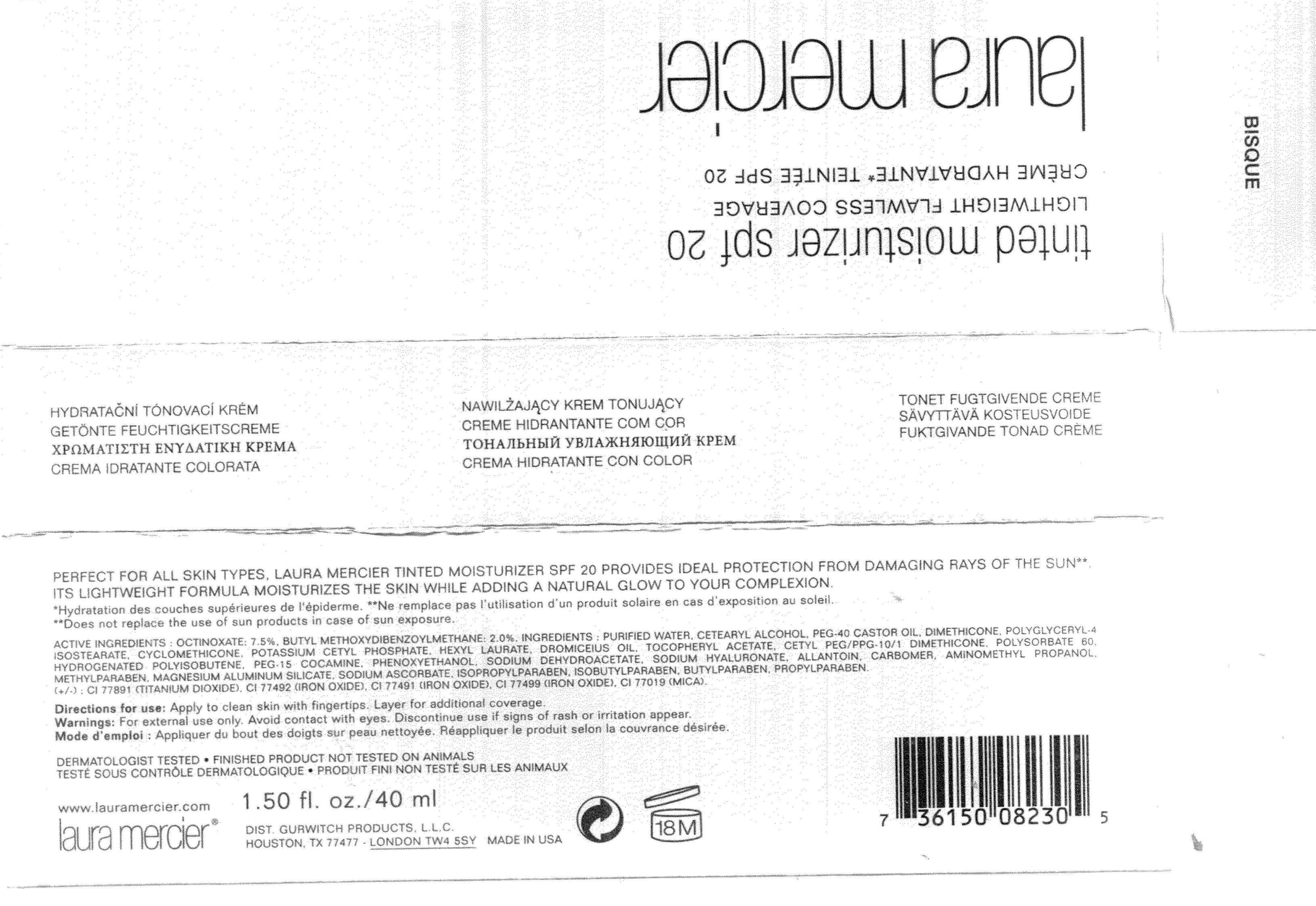 DRUG LABEL: Tinted Moisturizer SPF 20 Bisque 
NDC: 65342-1390 | Form: CREAM
Manufacturer: Gurwitch Products, L.L.C.
Category: otc | Type: HUMAN OTC DRUG LABEL
Date: 20110502

ACTIVE INGREDIENTS: Octinoxate 3 mL/40 mL; Avobenzone 0.8 mL/40 mL
INACTIVE INGREDIENTS: Water; Dimethicone; CYCLOMETHICONE 5  ; POLYGLYCERYL-4 ISOSTEARATE; CETOSTEARYL ALCOHOL; HEXYL LAURATE; .ALPHA.-TOCOPHEROL ACETATE, D-; SODIUM DEHYDROACETATE; HYALURONATE SODIUM; ALLANTOIN; SODIUM ASCORBATE; POLYSORBATE 60; PHENOXYETHANOL; METHYLPARABEN; PROPYLPARABEN; BUTYLPARABEN; ISOPROPYLPARABEN; ISOBUTYLPARABEN; AMINOMETHYLPROPANOL; LINALOOL, (+/-)- 

ACTIVE INGREDIENT

Octinoxate (7.5%) , Avobenzone (2.0%)

WARNINGS

WARNINGS : FOR EXTERNAL USE ONLY.AVOID CONTACT WITH EYES. IF CONTACT OCCURS. RINSE THOROUGH WITH WATER.

Keep out of reach of children.

INDICATIONS AND USAGE

Direction for use : Apply to clean skin with fingertips. Layer for additional coverage.

INACTIVE INGREDIENT

Other Ingredients : Water ,Cetearyl Alcohol , PEG-40 Castor Oil ,Dimethicone , Polyglyceryl-4 Isostearate , Cyclomethicone , Potassium Cetyl Phosphate , Hexyl Laurate , Dromiceius Oil ,Tocopheryl Acetate ,Cetyl PEG/PPG-10/1 Dimethicone ,Polysorbate 60 ,Hydrogenated Polyisobutene , PEG-15 Cocamine , Phenoxyethanol ,Sodium Dehydroacetate ,Sodium Hyaluronate ,Allantoin ,Carbomer ,

Aminomethyl Propanol , Methylparaben ,Magenesium Aluminu Silicate, Sodium Ascorbate , Isopropylparaben , Isobutylparaben , Butylpraben ,Propylparaben ,

(+/-) : CI 77891 (Titanium Dioxide) , CI 77492 (Iron Oxide) , CI 77491 (Iron Oxide) , CI 77499 (Iron Oxide) , CI 77019 (Mica)